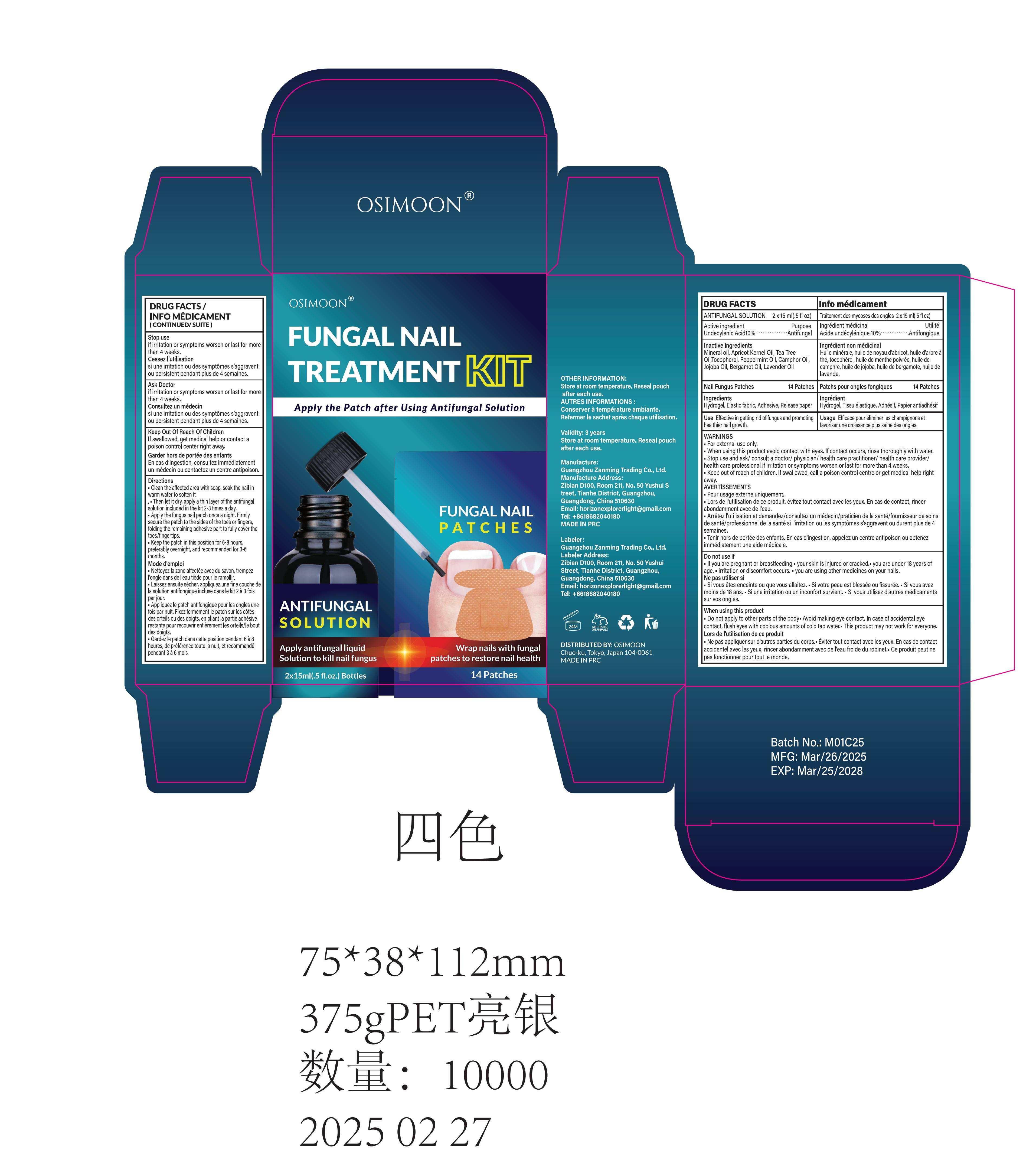 DRUG LABEL: Osimoon Fungal Nail Treatment Kit
NDC: 85150-008 | Form: LIQUID
Manufacturer: Guangzhou Zanming Trading Co., Ltd.
Category: otc | Type: HUMAN OTC DRUG LABEL
Date: 20250509

ACTIVE INGREDIENTS: UNDECYLENIC ACID 10 g/100 mL
INACTIVE INGREDIENTS: PEPPERMINT OIL; LAVENDER OIL; 2-(2'-HYDROXYTETRACOSANOYLAMINO)-OCTADECANE-1,3,4-TRIOL, (2S,3S,4R,2'R)-; APRICOT KERNEL OIL; POWDERED CELLULOSE; TEA TREE OIL; JOJOBA OIL; TESTOSTERONE; BERGAMOT OIL; DIETHYLENE GLYCOL ABIETATE; TOCOPHEROL; CAMPHOR OIL; MINERAL OIL

85150-008

Active Ingredient

Undecylenic Acid 10% W/W

Purpose

Antifungal

Use

Effective in getting rid of fungus and promoting healthier nail growth.

Warnings

• For external use only.
• When using this product avoid contact with eyes. If contact occurs, rinse thoroughly with water.
• Stop use and ask/ consult a doctor/ physician/ health care practitioner/ health care provider/ health care professional if irritation or symptoms worsen or last for more than 4 weeks.
• Keep out of reach of children. If swallowed, call a poison control centre or get medical help right away.

Do not use

• If you are pregnant or breastfeeding
• your skin is injured or cracked.
• you are under 18 years of age.
• irritation or discomfort occurs.
• you are using other medicines on your nails.

When Using

• Do not apply to other parts of the body.
• Avoid making eye contact. In case of accidental eye contact, flush eyes with copious amounts of cold tap water.
• This product may not work for everyone.

Stop Use

if irritation or symptoms worsen or last for more than 4 weeks.

Ask Doctor

if irritation or symptoms worsen or last for more than 4 weeks.

Keep Oot Of Reach Of Children

If swallowed, get medical help or contact a poison control center right away.

Directions

• Clean the affected area with soap, soak the nail in warm water to soften it.
• Then let it dry, apply a thin layer of the antifungal solution included in the kit 2-3 times a day.
• Apply the fungus nail patch once a night. Firmly secure the patch to the sides of the toes or fingers, folding the remaining adhesive part to fully cover the toes/fingertips.
• Keep the patch in this position for 6-8 hours, preferably overnight, and recommended for 3-6 months.

Other information

Store at room temperature. Reseal pouch after each use.

Inactive ingredients

Mineral oil, Apricot Kernel Oil, Tea Tree Oil,Tocopherol, Peppermint Oil, Camphor Oil, Jojoba Oil, Bergamot Oil, Lavender Oil, Hydrogel, Elastic fabric, Adhesive, Release paper